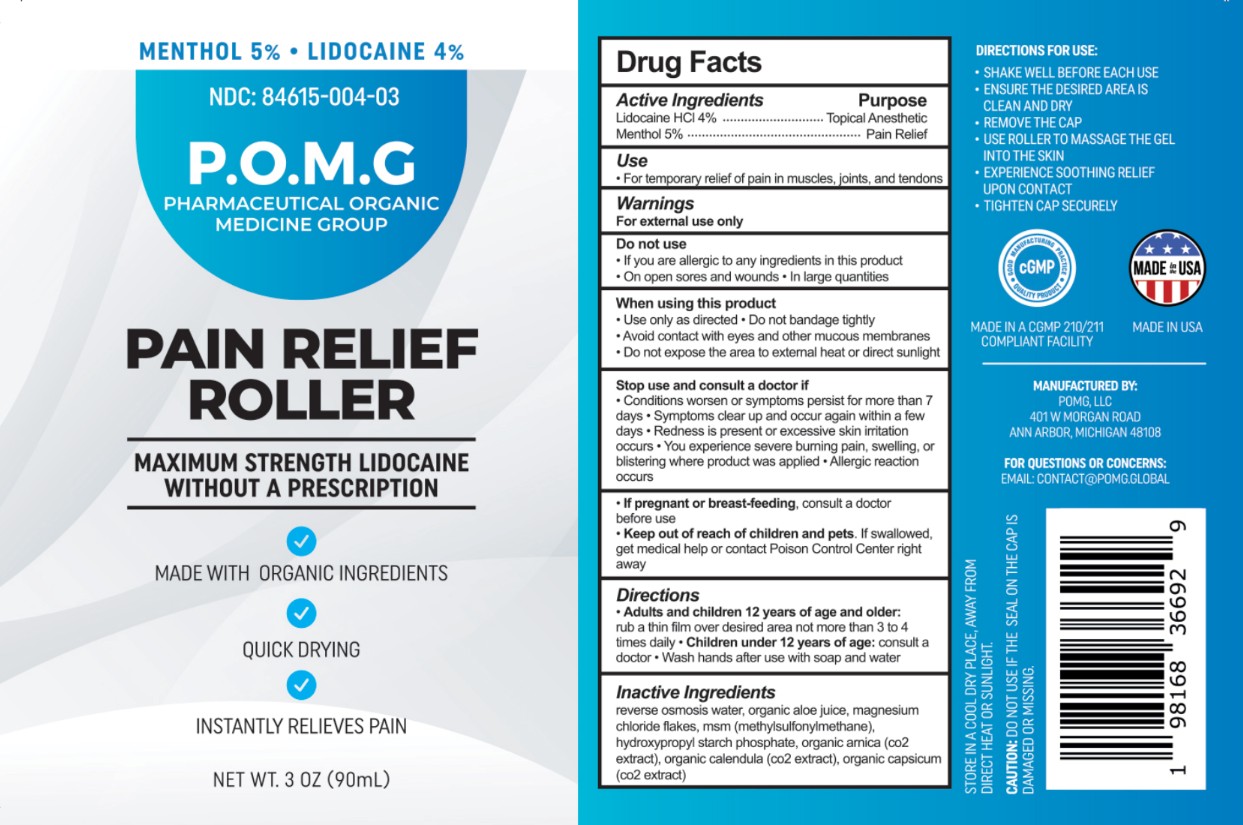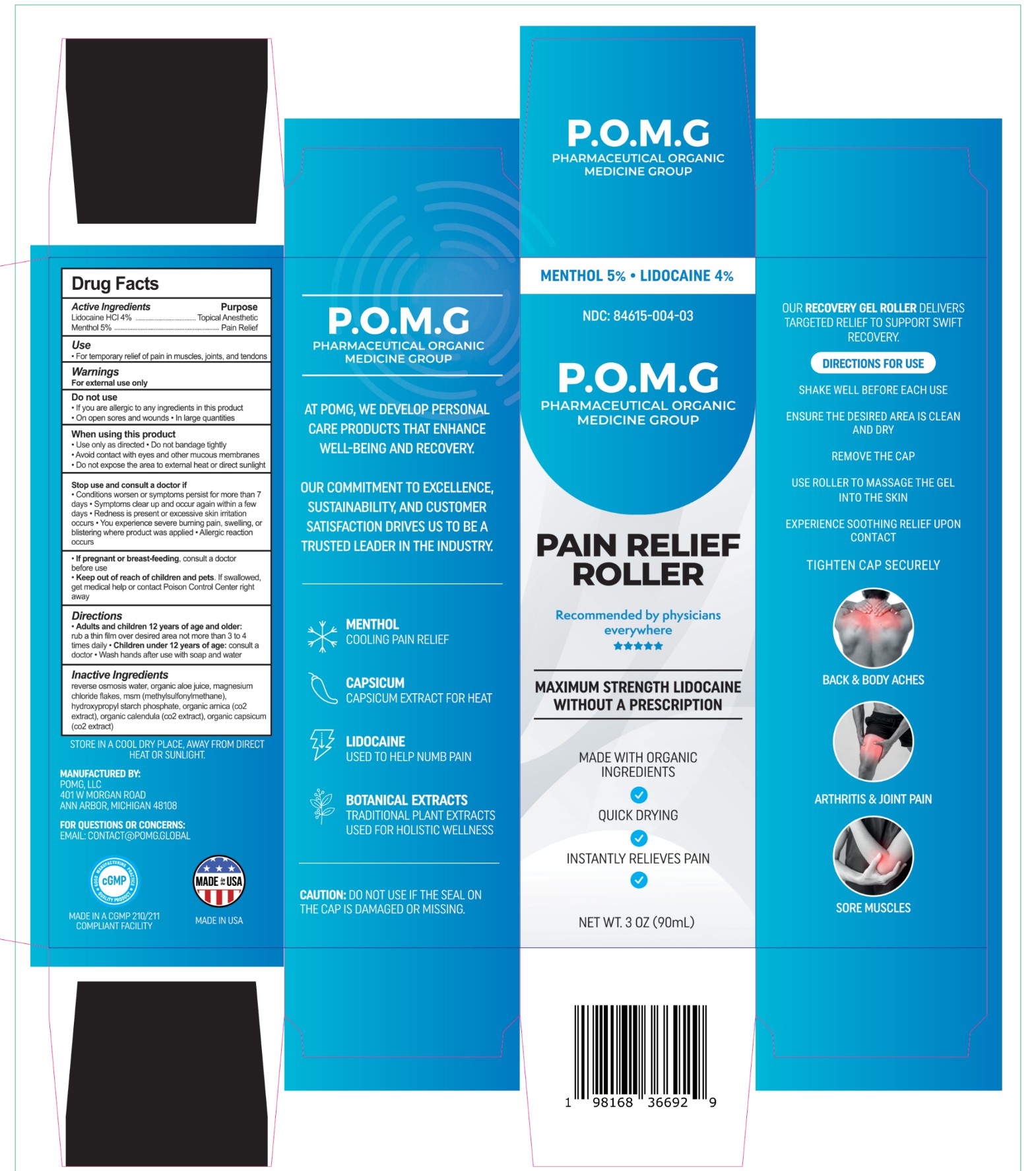 DRUG LABEL: POMG PAIN RELIEF ROLLER
NDC: 84615-004 | Form: GEL
Manufacturer: POMG LLC
Category: otc | Type: HUMAN OTC DRUG LABEL
Date: 20260107

ACTIVE INGREDIENTS: MENTHOL 50 mg/1 mL; LIDOCAINE HYDROCHLORIDE 40 mg/1 mL
INACTIVE INGREDIENTS: ARNICA MONTANA FLOWER; HYDROXYPROPYL CORN STARCH (5% SUBSTITUTION BY WEIGHT); CAPSICUM; MAGNESIUM CHLORIDE; CALENDULA OFFICINALIS FLOWER; WATER; ALOE VERA LEAF; DIMETHYL SULFONE

POMG PAIN RELIEF ROLLER

Active Ingredients

Lidocaine HCl 4%

Menthol 5%

Purpose

Lidocaine HCl 4% ……….…Topical Anesthetic

Menthol 5% ………………... Pain Relief

Use

- For temporary relief of pain in muscles, joints, and tendons

Warnings

For external use only

Do not use

• If you are allergic to any ingredients in this product

• On open sores and wounds

• In large quantities

When using this product

• Use only as directed

• Do not bandage tightly

• Avoid contact with eyes and other mucous membranes

• Do not expose the area to external heat or direct sunlight

Stop use and consult a doctor if

• Conditions worsen or symptoms persist for more than 7 days

• Symptoms clear up and occur again within a few days

• Redness is present or excessive skin irritation occurs

• You experience severe burning pain, swelling, or blistering where product was applied

• Allergic reaction occurs

PREGNANCY OR BREAST FEEDING

• If pregnant or breast-feeding, consult a doctor before use

• Keep out of reach of children and pets. If swallowed, get medical help or contact Poison Control Center right away

Directions

• Adults and children 12 years of age and older:

rub a thin film over desired area not more than 3 to 4 times daily

• Children under 12 years of age: consult a doctor

• Wash hands after use with soap and water

INACTIVE INGREDIENT

reverse osmosis water, organic aloe juice, magnesium chloride flakes, msm (methylsulfonylmethane), hydroxypropyl starch phosphate, organic arnica (co2 extract), organic calendula (co2 extract), organic capsicum (co2 extract)

PACKAGE LABEL

Menthol 5% Lidocaine 4%

NDC: 84615-004-03

P.O.M.G

Pharmaceutical Organic Medicine Group

Pain Relief Roller

Recommened by physicians everywhere

Maximum Strength Lidocaine

Without a Prescription

Made with Organic Ingredients

Quick Drying

Instantly Relieves Pain

Net Wt. 3 OZ (90mL)